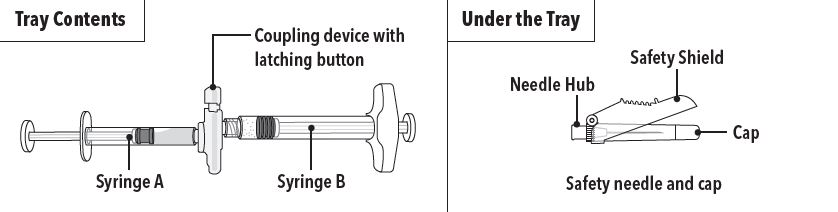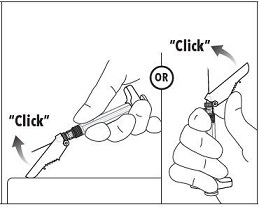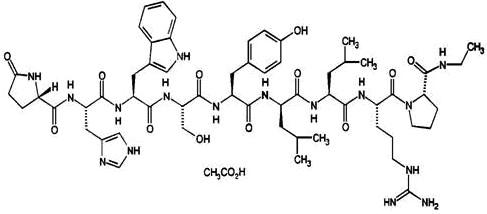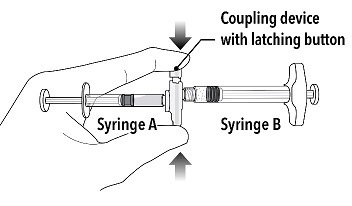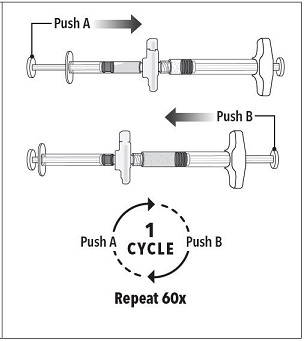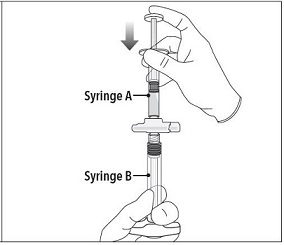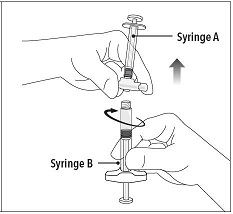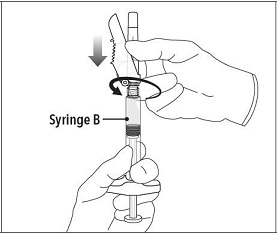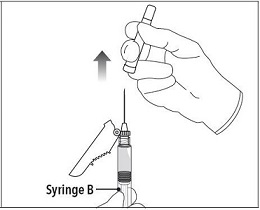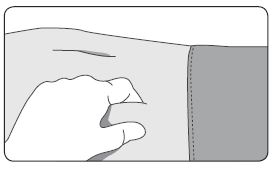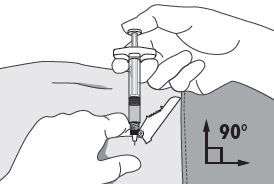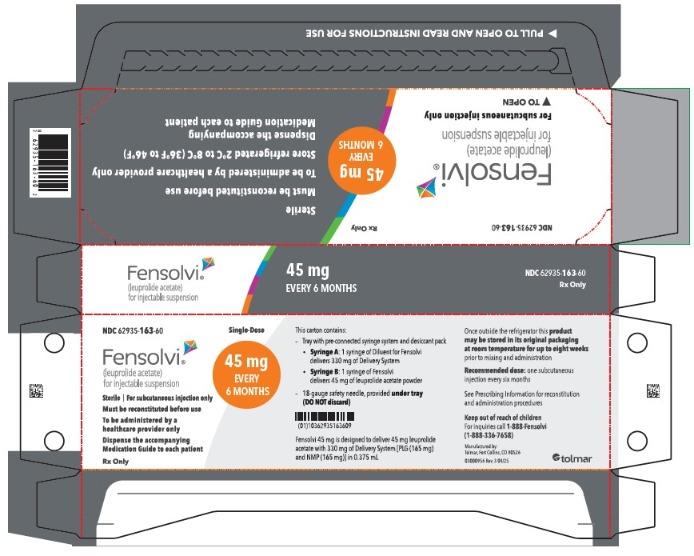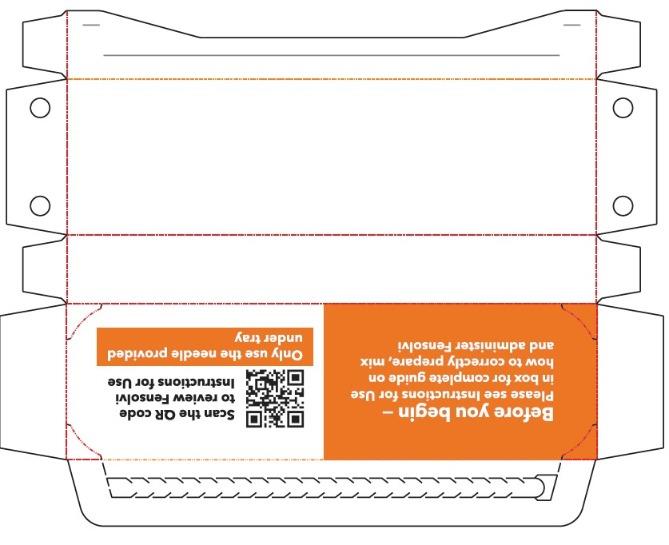 DRUG LABEL: Fensolvi
NDC: 62935-163 | Form: INJECTION, SUSPENSION, EXTENDED RELEASE
Manufacturer: TOLMAR Inc.
Category: prescription | Type: HUMAN PRESCRIPTION DRUG LABEL
Date: 20250925

ACTIVE INGREDIENTS: LEUPROLIDE ACETATE 45 mg/0.375 mL
INACTIVE INGREDIENTS: METHYL PYRROLIDONE 165 mg/0.375 mL; POLY(DL-LACTIC-CO-GLYCOLIC ACID), (85:15; 23000 MW) 165 mg/0.375 mL

HIGHLIGHTS OF PRESCRIBING INFORMATION

These highlights do not include all the information needed to use FENSOLVI® safely and effectively. See full prescribing information for FENSOLVI.
FENSOLVI (leuprolide acetate) for injectable suspension, for subcutaneous use
Initial U.S. Approval: 1985

RECENT MAJOR CHANGES

Warnings and Precautions, Severe Cutaneous Adverse Reactions (5.4) 09/2025
Dosage and Administration (2.3) 10/2024

1 INDICATIONS AND USAGE

FENSOLVI is a gonadotropin releasing hormone (GnRH) agonist indicated for the treatment of pediatric patients 2 years of age and older with central precocious puberty.

2 DOSAGE AND ADMINISTRATION

- Must be administered by a healthcare provider. (2.1)
- The dose of FENSOLVI is 45 mg administered by subcutaneous injection once every six months. (2.1)
- Monitor response to FENSOLVI with a GnRH agonist stimulation test, basal serum luteinizing hormone (LH) levels or serum concentration of sex steroid levels at 1 to 2 months following initiation of therapy and as needed to confirm adequate suppression of pituitary gonadotropins, sex steroids, and progression of secondary sexual characteristics. (2.2)
- Measure height every 3 to 6 months and monitor bone age periodically. (2.2)
- See Full Prescribing Information for reconstitution and administration instructions. (2.3, 2.4)

3 DOSAGE FORMS AND STRENGTHS

- For injectable suspension: 45 mg of leuprolide acetate. (3)

4 CONTRAINDICATIONS

- Hypersensitivity reactions (4)
- Pregnancy (4, 8.1)

5 WARNINGS AND PRECAUTIONS

- Initial Rise of Gonadotropins and Sex Steroid Levels: During the early phase of therapy, gonadotropins and sex steroids rise above baseline because of the initial stimulatory effect of the drug. Therefore, an increase in clinical signs and symptoms of puberty including vaginal bleeding may be observed during the first weeks of therapy or after subsequent doses. Instruct patients and caregivers to notify the physician if these symptoms continue beyond the second month after FENSOLVI administration. (5.1)
- Psychiatric events: Have been reported in patients taking GnRH agonists. Events include emotional lability, such as crying, irritability, impatience, anger, and aggression. Monitor for development or worsening of psychiatric symptoms. (5.2)
- Convulsions: Have been observed in patients with or without a history of seizures, epilepsy, cerebrovascular disorders, central nervous system anomalies or tumors, and in patients on concomitant medications that have been associated with convulsions. (5.3)
- Severe Cutaneous Adverse Reactions (SCARs): Have been reported in patients receiving GnRH agonists, including leuprolide products. Interrupt FENSOLVI if signs and symptoms of SCARs develop. Permanently discontinue FENSOLVI if a SCAR is confirmed (5.4).
- Pseudotumor Cerebri (Idiopathic Intracranial Hypertension): Have been reported in pediatric patients receiving GnRH agonists, including leuprolide acetate. Monitor patients for headache, papilledema, and blurred vision. (5.5)

6 ADVERSE REACTIONS

- The most common adverse reactions (≥5%) were: injection site pain, nasopharyngitis, pyrexia, headache, cough, abdominal pain, injection site erythema, nausea, constipation, vomiting, upper respiratory tract infection, bronchospasm, productive cough, and hot flush. (6.1)

To report SUSPECTED ADVERSE REACTIONS, contact Tolmar at 1-844-4TOLMAR (1-844-486-5627) or FDA at 1-800-FDA-1088 or www.fda.gov/medwatch.

FULL PRESCRIBING INFORMATION

RECENT MAJOR CHANGES

Dosage and Administration (2) 05/2022

Warnings and Precautions (5.4) 03/2022

1 INDICATIONS AND USAGE

FENSOLVI® is indicated for the treatment of pediatric patients 2 years of age and older with central precocious puberty (CPP).

2 DOSAGE AND ADMINISTRATION

2.1 Dosing Information

FENSOLVI must be administered by a healthcare provider.

The dose of FENSOLVI is 45 mg administered by subcutaneous injection once every six months.

Discontinue FENSOLVI treatment at the appropriate age of onset of puberty.

2.2 Monitoring

Monitor response to FENSOLVI with a GnRH agonist stimulation test, basal serum luteinizing hormone (LH) levels or serum concentration of sex steroid levels at 1 to 2 months following initiation of therapy and as needed to confirm adequate suppression of pituitary gonadotropins, sex steroids, and progression of secondary sexual characteristics. Measure height (for calculation of growth velocity) every 3 to 6 months and monitor bone age periodically.

Noncompliance with drug regimen or inadequate dosing may lead to gonadotropins and/or sex steroids increasing above prepubertal levels resulting in inadequate control of the pubertal process. If the dose of FENSOLVI is not adequate, switching to an alternative GnRH agonist for the treatment of CPP with the ability for dose adjustment may be necessary.

2.3 Reconstitution Instructions

Use aseptic technique including gloves for reconstitution and administration. Allow the product to reach room temperature before reconstitution to allow for easier administration. Once reconstituted, the concentration is 45 mg/0.375 mL. Administer the product within 30 minutes or discard.

FENSOLVI is packaged in a carton containing:

- Tray containing pre-connected syringe system and desiccant pack
- Prescribing information
- Sterile safety needle and cap (located under the tray in carton)

Follow the detailed instructions below to ensure correct preparation of FENSOLVI prior to administration:

Step 1

On a clean field open the tray by tearing off the foil from the corner and remove the contents. Discard the desiccant pack. Remove the pre-connected syringe system from the tray. Open the sterile safety needle package by peeling back the paper tab. Note: Syringe A and Syringe B should not be lined-up yet. The product should only be administered with the co-packaged, sterile safety needle.

Step 2

Grasp the latching button on the coupling device with your finger and thumb and press until you hear a snapping sound. The two syringes will be aligned.

Do not bend the pre-connected syringe system.

Step 3

Holding the syringes in a horizontal position, transfer the liquid contents of Syringe A into the leuprolide acetate powder contained in Syringe B. Thoroughly mix the product for 60 cycles by pushing the contents back and forth between both syringes to obtain a uniform suspension.

- A cycle is one push of the Syringe A plunger and one push of the Syringe B plunger.
- When thoroughly mixed, the suspension will appear colorless to pale yellow.

Note: Product must be mixed as described; shaking will NOT provide adequate mixing. Do not bend.

Step 4

After mixing, hold the syringes vertically (upright) with Syringe B (wide syringe) on the bottom. The syringes should remain securely coupled. Transfer all of the mixed product into Syringe B by depressing the Syringe A plunger and slightly withdrawing the Syringe B plunger.

Step 5

While ensuring the Syringe A plunger is fully pushed down, hold the coupling device and unscrew Syringe B. This will disconnect Syringe B from the coupling device. Syringe A will remain attached to the coupling device.

Note: Small air bubbles will remain in the formulation – this is acceptable.

Do not purge the air bubbles from Syringe B as product may be lost!

Step 6

Continue to hold Syringe B upright with the open end at the top. Hold back the white plunger on Syringe B to prevent loss of the product, and attach the safety needle and cap (the safety needle is located under the tray). Gently screw clockwise with approximately a three-quarter turn until the safety needle and cap are secure.

Do not overtighten, as the needle hub may become damaged which could result in leakage of the product during injection. The safety shield may also be damaged if the safety needle and cap are screwed with too much force.

Step 7

Move the safety shield away from the needle and towards the syringe.

Pull off the cap immediately prior to administration.

Note: Should the needle hub appear to be damaged, or leak, do not use the product. If the needle hub is damaged or leakage is observed, use a new FENSOLVI carton.

2.4 Administration Instructions

1. Select an injection site on the abdomen, upper buttocks, or another location with adequate amounts of subcutaneous tissue that does not have excessive pigment, nodules, lesions, or hair and hasn’t recently been used.

2. Cleanse the injection-site area with an alcohol swab (not enclosed).

3. Using the thumb and forefinger, grab and bunch the area of skin around the injection site.

4. Using your dominant hand, insert the needle quickly at a 90° angle to the skin surface. The depth of penetration will depend on the amount and fullness of the subcutaneous tissue and the length of the needle. After the needle is inserted, release the skin.

5. Inject the drug using a slow, steady push and press down on the plunger until the syringe is empty.

Make sure all the drug has been injected before removing the needle.

6. Withdraw the needle quickly at the same 90° angle used for insertion.

7. Immediately following the withdrawal of the needle, activate the safety shield using a finger/thumb or flat surface and push until it completely covers the needle tip and locks into place.

8. An audible and tactile “click” verifies a locked position.

9. Check to confirm the safety shield is fully engaged. Discard all components safely in an appropriate biohazard container.

3 DOSAGE FORMS AND STRENGTHS

For injectable suspension, 45 mg of leuprolide acetate.

Each FENSOLVI carton contains:

- Pre-connected syringe system consisting of syringe A and syringe B connected using a coupling device.
  - Syringe A contains diluent for reconstitution (in situ polymeric extended release technology) in a prefilled syringe.
  - Syringe B contains 45 mg lyophilized leuprolide acetate powder in a single-dose prefilled syringe.
- Sterile safety needle and cap
- Desiccant
- Prescribing information

4 CONTRAINDICATIONS

- Hypersensitivity to GnRH, GnRH agonists or any of the components of FENSOLVI. Anaphylactic reactions to synthetic GnRH or GnRH agonists have been reported [see Adverse Reactions (6.2)].
- Pregnancy: FENSOLVI may cause fetal harm [see Use in Specific Populations (8.1)].

5 WARNINGS AND PRECAUTIONS

5.1 Initial Rise of Gonadotropins and Sex Steroid Levels

During the early phase of therapy, gonadotropins and sex steroids rise above baseline because of the initial stimulatory effect of the drug [see Clinical Pharmacology (12.2)]. Therefore, an increase in clinical signs and symptoms of puberty including vaginal bleeding may be observed during the first weeks of therapy or after subsequent doses [see Adverse Reactions (6)]. Instruct patients and caregivers to notify the physician if these symptoms continue beyond the second month after FENSOLVI administration.

5.2 Psychiatric Events

Psychiatric events have been reported in patients taking GnRH agonists, including leuprolide acetate. Postmarketing reports with this class of drugs include symptoms of emotional lability, such as crying, irritability, impatience, anger, and aggression. Monitor for development or worsening of psychiatric symptoms during treatment with FENSOLVI [see Adverse Reactions (6.1, 6.2)].

5.3 Convulsions

Postmarketing reports of convulsions have been observed in patients receiving GnRH agonists, including leuprolide acetate. These included patients with a history of seizures, epilepsy, cerebrovascular disorders, central nervous system anomalies or tumors, and patients on concomitant medications that have been associated with convulsions such as bupropion and SSRIs. Convulsions have also been reported in patients in the absence of any of the conditions mentioned above [see Adverse Reactions (6.2)].

5.4 Severe Cutaneous Adverse Reactions

Severe cutaneous adverse reactions (SCAR) have been reported in patients receiving GnRH agonists, including leuprolide products [see Adverse Reactions (6.2)]. These reactions include Stevens–Johnson syndrome/toxic epidermal necrolysis (SJS/TEN), drug reaction with eosinophilia and systemic symptoms (DRESS), and acute generalized exanthematous pustulosis (AGEP), including cases with visceral involvement and/or requiring skin grafts.

Monitor patients for signs and symptoms of SCARs such as fever, flu-like symptoms, mucosal lesions, progressive skin rash or lymphadenopathy. Advise patients and caregivers of the signs and symptoms of SCARs.

If a SCAR is suspected, interrupt FENSOLVI. Consult a healthcare provider with expertise in the diagnosis and management of SCARs. If a diagnosis of SCARs is confirmed, permanently discontinue FENSOLVI.

5.5 Pseudotumor Cerebri (Idiopathic Intracranial Hypertension)

Pseudotumor cerebri (idiopathic intracranial hypertension) have been reported in pediatric patients receiving GnRH agonists, including leuprolide acetate. Monitor patients for signs and symptoms of pseudotumor cerebri, including headache, papilledema, blurred vision, diplopia, loss of vision, pain behind the eye or pain with eye movement, tinnitus, dizziness, and nausea [see Adverse Reactions (6.2)].

6 ADVERSE REACTIONS

The following serious adverse reactions are described here and elsewhere in the label:

- Initial rise in gonadotropin and sex steroid levels [see Warnings and Precautions (5.1)]
- Psychiatric Events [see Warnings and Precautions (5.2)]
- Convulsions [see Warnings and Precautions (5.3)]
- Severe Cutaneous Adverse Reactions [see Warnings and Precautions (5.4)]
- Pseudotumor Cerebri (Idiopathic Intracranial Hypertension) [see Warnings and Precautions (5.5)]

6.1 Clinical Trials Experience

Because clinical studies are conducted under widely varying conditions, adverse reaction rates observed in the clinical trials of a drug cannot be directly compared to rates in the clinical trials of another drug and may not reflect the rates observed in practice.

FENSOLVI was evaluated in an uncontrolled, open-label, single-arm clinical trial in which 64 pediatric patients with CPP received at least one dose of FENSOLVI. The age ranged from 4 to 9 years at start of treatment; 62 patients were female and 2 were male; 53% White; 23% Black; 8% American Indian or Alaska Native; 5% Asian; 2% Native Hawaiian or Other Pacific Islander. 56% of the subjects self-identified as Hispanic or Latino ethnicity. Adverse reactions that occurred in ≥ 5% of patients are shown in Table 1.

Table 1: Adverse Reactions Occurring in ≥ 5% of Patients Treated with FENSOLVI in an Open-Label, Single-Arm Trial

Adverse Reactions | % of Patients (N=64)
Injection site pain | 31
Nasopharyngitis | 22
Pyrexia | 17
Headache | 16
Cough | 13
Abdominal pain | 9
Injection site erythema | 9
Nausea | 8
Constipation | 6
Vomiting | 6
Upper respiratory tract infection | 6
Bronchospasm | 6
Productive cough | 6
Hot flush | 5

Other Adverse Reactions:

Psychiatric

Emotional disorder (2%) and irritability (2%)

6.2 Postmarketing Experience

The following adverse reactions have been identified during post-approval use of FENSOLVI or GnRH agonists. Because these reactions are reported voluntarily from a population of uncertain size, it is not always possible to reliably estimate their frequency or establish a causal relationship to drug exposure.

Allergic Reactions: anaphylactic, rash, urticaria, and photosensitivity reactions.

General: chest pain, weight increase, weight decrease, decreased appetite, fatigue.

Laboratory Abnormalities: decreased WBC.

Metabolic: diabetes mellitus.

Musculoskeletal and Connective Tissue: arthralgia, epiphysiolysis, muscle spasms, myalgia.

Neurologic: neuropathy peripheral, convulsion, paralysis, insomnia, pseudotumor cerebri (idiopathic intracranial hypertension).

Psychiatric: emotional lability, such as crying, irritability, impatience, anger and aggression, depression, including rare reports of suicidal ideation and attempt. Many, but not all, of these patients had a history of psychiatric illness or other comorbidities with an increased risk of depression.

Skin and Subcutaneous Tissue: injection site reactions including induration and abscess, flushing, hyperhidrosis, erythema multiforme, bullous dermatitis, dermatitis exfoliative, drug reaction with eosinophilia and systemic symptoms, Stevens-Johnson syndrome and toxic epidermal necrolysis, and acute generalized exanthematous pustulosis.

Reproductive System: vaginal bleeding, breast enlargement.

Vascular: hypertension, hypotension.

Respiratory: dyspnea.

8 USE IN SPECIFIC POPULATIONS

8.1 Pregnancy

Risk Summary

FENSOLVI is contraindicated in pregnancy [see Contraindications (4)].

FENSOLVI may cause fetal harm based on findings from animal studies and the drug’s mechanism of action [see Clinical Pharmacology (12.1)]. The available data from published clinical studies and case reports and from the pharmacovigilance database on exposure to leuprolide acetate during pregnancy are insufficient to assess the risk of major birth defects, miscarriage, or adverse maternal or fetal outcomes. Based on animal reproduction studies, leuprolide acetate may be associated with an increased risk of pregnancy complications, including early pregnancy loss and fetal harm. In animal reproduction studies, subcutaneous administration of leuprolide acetate to rabbits during the period of organogenesis caused embryo-fetal toxicity, decreased fetal weights and a dose-dependent increase in major fetal abnormalities in animals at doses less than the recommended human dose based on body surface area using an estimated daily dose. A similar rat study also showed increased fetal mortality and decreased fetal weights but no major fetal abnormalities at doses less than the recommended human dose based on body surface area using an estimated daily dose (see Data).

The estimated background risk of major birth defects and miscarriage for the indicated population is unknown. In the US general population, the estimated background risk of major birth defects and miscarriage in clinically recognized pregnancies is 2% to 4% and 15% to 20%, respectively.

Data

Animal Data

When administered on day 6 of pregnancy at test dosages of 0.00024 mg/kg, 0.0024 mg/kg, and 0.024 mg/kg (1/3255 to 1/33 of the human dose) to rabbits, leuprolide acetate produced a dose-related increase in major fetal abnormalities. Similar studies in rats failed to demonstrate an increase in fetal malformations. There was increased fetal mortality and decreased fetal weights with the two higher doses of leuprolide acetate in rabbits and with the highest dose (0.024 mg/kg) in rats.

8.2 Lactation

Risk Summary

There are no data on the presence of leuprolide acetate in either animal or human milk, the effects on the breastfed infants, or the effects on milk production. The developmental and health benefits of breastfeeding should be considered along with the mother’s clinical need for FENSOLVI and any potential adverse reactions on the breastfed infant from FENSOLVI or from the underlying maternal condition.

8.3 Females and Males of Reproductive Potential

Pregnancy Testing

Exclude pregnancy in women of reproductive potential prior to initiating FENSOLVI if clinically indicated [see Use in Specific Populations (8.1)].

Contraception

Females

FENSOLVI may cause embryo-fetal harm when administered during pregnancy. FENSOLVI is not a contraceptive. If contraception is indicated, advise females of reproductive potential to use a non-hormonal method of contraception during treatment with FENSOLVI [see Use in Specific Populations (8.1)].

Infertility

Based on its pharmacodynamic effects of decreasing secretion of gonadal steroids, fertility is expected to be decreased while on treatment with FENSOLVI. Clinical and pharmacologic studies in adults (>18 years) with leuprolide acetate and similar analogs have shown reversibility of fertility suppression when the drug is discontinued after continuous administration for periods of up to 24 weeks [see Clinical Pharmacology (12.1)].

There is no evidence that pregnancy rates are affected following discontinuation of FENSOLVI.

Animal studies (prepubertal and adult rats and monkeys) with leuprolide acetate and other GnRH analogs have shown functional recovery of fertility suppression.

8.4 Pediatric Use

The safety and effectiveness of FENSOLVI for the treatment of CPP has been established in pediatric patients 2 years of age and older. Use of FENSOLVI for this indication is supported by evidence from an adequate and uncontrolled open-label, single-arm study of 64 pediatric patients with CPP with an age range of 4 to 9 years [see Clinical Studies (14)]. The safety and effectiveness of FENSOLVI have not been established in pediatric patients less than 2 years old.

10 OVERDOSAGE

No specific antidotes for FENSOLVI are known. Contact Poison Control (1-800-222-1222) for latest recommendations.

11 DESCRIPTION

FENSOLVI for injectable suspension is a sterile polymeric matrix formulation of leuprolide acetate, a GnRH agonist, for subcutaneous use. It is designed to deliver leuprolide acetate at a controlled rate over a six-month therapeutic period.

Leuprolide acetate is a synthetic nonapeptide analog of naturally occurring gonadotropin releasing hormone. The analog possesses greater potency than the natural hormone. The chemical name is 5-oxo-L-prolyl-L-histidyl-L-tryptophyl-L-seryl-L-tyrosyl-D-leucyl-L-leucyl-L-arginyl-N-ethyl-L-prolinamide acetate (salt) with the following structural formula:

FENSOLVI is supplied as a pre-connected syringe system. Immediately prior to administration, the content of the pre-connected syringe system are mixed until homogenous. FENSOLVI is administered subcutaneously, where it forms a solid drug delivery depot.

Syringe A contains the in situ polymeric extended release technology consisting of a biodegradable poly (DL-lactide-co-glycolide) (PLG) polymer formulation dissolved in a biocompatible solvent, N-methyl-2pyrrolidone (NMP) and syringe B contains the leuprolide acetate.

Refer to Table 2 for the delivery system composition and reconstituted product formulation for FENSOLVI product.

Table 2: FENSOLVI Delivery System Composition and Reconstituted Product Formulation

In situ polymeric extended release technology | Polymer | PLG
In situ polymeric extended release technology | Polymer description | Copolymer with hexanediol
In situ polymeric extended release technology | Polymer DL-lactide to glycolide molar ratio | 85:15
Reconstituted Product | Polymer delivered | 165 mg
 | NMP delivered | 165 mg
 | Leuprolide acetate delivered | 45 mg
 | Approximate leuprolide free base equivalent | 42 mg
 | Approximate administered formulation weight | 375 mg
 | Approximate injection volume | 0.375 mL

12 CLINICAL PHARMACOLOGY

12.1 Mechanism of Action

Leuprolide acetate, a GnRH agonist, acts as a potent inhibitor of gonadotropin secretion (LH and follicle stimulating hormone (FSH)) when given continuously in therapeutic doses. Following an initial stimulation of GnRH receptors, chronic administration of leuprolide acetate results in downregulation of GnRH receptors, reduction in release of LH, FSH and consequent suppression of ovarian and testicular production of estradiol and testosterone respectively. This inhibitory effect is reversible upon discontinuation of drug therapy.

12.2 Pharmacodynamics

In the clinical trial evaluating FENSOLVI in pediatric patients with CPP, there was a transient surge in circulating levels of LH, FSH, estradiol and testosterone following the first administration. A decrease in basal and GnRH agonist-stimulated LH and FSH levels along with reductions in basal estradiol and testosterone were observed after repeat administration.

12.3 Pharmacokinetics

Absorption

After an initial subcutaneous injection of FENSOLVI 45 mg in pediatric patients 4 to 9 years of age with CPP, leuprolide levels peaked 4 hours postdose with a mean Cmax of 212.3 ng/mL. Absorption occurred in two phases, a burst phase followed by a plateau phase. The mean plateau serum leuprolide level from 4 to 48 weeks was approximately 0.37 ng/mL with a range of 0.18 to 0.63 ng/mL. There was no accumulation of leuprolide after the second dose.

Distribution

The distribution of leuprolide following FENSOLVI administration was not evaluated in pediatric patients. The mean steady-state volume of distribution of leuprolide following intravenous bolus administration to healthy male volunteers was 27 L.

In vitro binding of leuprolide to human plasma proteins ranged from 43% to 49%.

Elimination

Metabolism

In rats and dogs, administration of ^14C-labeled leuprolide was shown to be metabolized to smaller inactive peptides: a pentapeptide (Metabolite I), tripeptides (Metabolites II and III), and a dipeptide (Metabolite IV). These fragments may be further catabolized.

In healthy male volunteers, a 1 mg bolus of leuprolide administered intravenously revealed that the mean systemic clearance was 8.34 L/h, with a terminal elimination half-life of approximately 3 hours based on a two-compartment model.

Upon administration with different leuprolide acetate formulations, the major metabolite of leuprolide acetate is a pentapeptide (M-1) metabolite.

Specific Populations

The pharmacokinetics of FENSOLVI in hepatically and renally impaired pediatric patients have not been determined.

13 NONCLINICAL TOXICOLOGY

13.1 Carcinogenesis, Mutagenesis, Impairment of Fertility

Two-year carcinogenicity studies were conducted with leuprolide acetate in rats and mice. In rats, a dose-related increase of benign pituitary hyperplasia and benign pituitary adenomas was noted at 24 months when the drug was administered subcutaneously at high daily doses (0.6 to 4 mg/kg). There was a significant but not dose-related increase of pancreatic islet-cell adenomas in females and of testicular interstitial cell adenomas in males (highest incidence in the low dose group). In mice, no leuprolide acetate-induced tumors or pituitary abnormalities were observed at a dose as high as 60 mg/kg for two years. Patients have been treated with leuprolide acetate for up to three years with doses as high as 10 mg/day and for two years with doses as high as 20 mg/day without demonstrable pituitary abnormalities. No carcinogenicity studies have been conducted with FENSOLVI.

Mutagenicity studies have been performed with leuprolide acetate using bacterial and mammalian systems. These studies provided no evidence of a mutagenic potential.

14 CLINICAL STUDIES

The efficacy of FENSOLVI was evaluated in an uncontrolled, open-label, single arm clinical trial in which 64 pediatric patients (62 females and 2 males, naïve to previous GnRH agonist treatment) with CPP received at least one dose of FENSOLVI at a dosing interval of 24 weeks and were observed for 12 months. The mean age was 7.5 years (range 4 to 9 years) at the start of treatment. In pediatric patients with CPP, FENSOLVI reduced stimulated and basal gonadotropins to prepubertal levels. Suppression of peak stimulated LH concentrations to <4 IU/L was achieved in 87% of pediatric patients by month 6 and in 86% of patients by month 12. Suppression of estradiol or testosterone concentration to prepubertal levels at the 6-month assessment was achieved in 97% and 100% of patients, respectively. Suppression of estradiol or testosterone was maintained at the 12-month assessment with 98% (55/56 females) and 50% (1/2 males) maintaining suppression. FENSOLVI arrested or reversed progression of clinical signs of puberty with reductions in growth velocity and bone age. Mean growth velocity decreased from 8.9 ± 13.1 cm/yr at 1 month to 6.9 ± 3.1 cm/yr at 6 months and to 6.4 ± 1.9 cm/yr at 12 months.

Table 3: Reproductive Hormone Levels in Pediatric Patients with CPP Treated with FENSOLVI 45 mg Every 6 Monthsa

 | % (n/N) of Patients Achieving Endpoints
Endpointb | Month 3 | Month 6 | Month 9 | Month 12
LH levels < 4 IU/L | 85 (51/60) | 87 (54/62)c | 85 (50/59) | 86 (50/58)
Estradiol levels < 73.4 pmol/L (< 20 pg/mL) | 98 (56/57) | 97 (58/60) | 98 (56/57) | 98 (55/56)
Testosterone levels < 1 nmol/L (< 28.4 ng/dL) | 100 (2/2) | 100 (2/2) | 100 (2/2) | 50 (1/2)
FSH levels < 2.5 IU/L | 62 (37/60) | 66 (41/62) | 44 (26/59) | 55(32/58)
aIntent-to-treat Population (N=62) bPost GnRH agonist stimulation cPrimary Efficacy Endpoint

Eight female patients out of 62 did not meet the primary efficacy criteria for LH <4 IU/L at 6 months. In four of the eight patients, the LH level at 6 months was between 4.2 and 4.8 IU/L. The remaining four patients had LH levels >5 IU/L. However, post stimulation estradiol was suppressed to prepubertal levels (<20 pg/mL) in seven of the eight patients at month 6 and was maintained through month 12.

16 HOW SUPPLIED/STORAGE AND HANDLING

For injectable suspension, 45 mg of leuprolide acetate (NDC 62935-163-60) supplied in a carton that contains:

- Tray containing pre-connected syringe system and desiccant pack
- Prescribing information
- Sterile safety needle and cap (located under the tray in carton)

Store refrigerated at 2°C to 8°C (36°F to 46°F).

Once outside the refrigerator, this product may be stored in its original packaging at room temperature 15°C to 30°C (59°F to 86°F) for up to eight weeks prior to reconstitution and administration.

17 PATIENT COUNSELING INFORMATION

Advise the patient to read the FDA-approved patient labeling (Medication Guide).

Symptoms After Initial FENSOLVI Administration

Inform patients and caregivers that during the early phase of therapy with FENSOLVI, gonadotropins and sex steroids rise above baseline because of the initial stimulatory effect of the drug. Therefore, an increase in clinical signs and symptoms of puberty may be observed. Instruct patients and caregivers to notify the physician if these symptoms continue beyond the second month after FENSOLVI administration [see Warnings and Precautions (5.1)].

Psychiatric Events

Inform patients and caregivers that psychiatric events have been reported in patients taking GnRH agonists, including leuprolide acetate. Events include emotional lability, such as crying, irritability, impatience, anger, and aggression. Instruct patients and caregivers to monitor for development or worsening of psychiatric symptoms including depression during treatment with FENSOLVI [see Warnings and Precautions (5.2)].

Convulsions

Inform patients and caregivers that reports of convulsions have been observed in patients receiving GnRH agonists, including leuprolide acetate. Patients with a history of seizures, epilepsy, cerebrovascular disorders, central nervous system anomalies or tumors, and patients on concomitant medications that have been associated with convulsions may be at increased risk [see Warnings and Precautions (5.3)].

Severe Cutaneous Adverse Reactions

Inform patients and/or caregivers that severe cutaneous adverse reactions (SCARs) may occur during treatment with FENSOLVI. Advise patients and/or caregivers to stop FENSOLVI and immediately contact their healthcare provider if they experience signs and symptoms of SCARs [see Warnings and Precautions (5.4)].

Pseudotumor Cerebri (Idiopathic Intracranial Hypertension)

Inform patients and caregivers that reports of pseudotumor cerebri (idiopathic intracranial hypertension) have been observed in pediatric patients receiving GnRH agonists, including leuprolide acetate. Advise patients and caregivers to monitor for headache, and vision issues such as blurred vision, double vision, loss of vision, pain behind the eye or pain with eye movement, ringing in the ears, dizziness, and nausea. Advise patients and caregivers to contact their healthcare provider if the patient develops any these symptoms. [see Warnings and Precautions (5.5)].

Injection Site Reactions

Inform patients and caregivers that injection site related adverse reactions may occur such as transient burning/stinging, pain, bruising, and redness. Advise patients to contact their healthcare provider if they experience rash or severe injection site reactions [see Adverse Reactions (6.1)].

Pregnancy

FENSOLVI is contraindicated in pregnancy. If the patient becomes pregnant while taking the drug, the patient should be informed of the potential risk to the fetus [see Use in Specific Populations (8.1)].

Compliance with the Dosing Schedule

Inform caregivers about the importance of adherence to the FENSOLVI dosing schedule of one injection every 24 weeks [see Dosage and Administration (2.1, 2.2)].

Manufactured by: Tolmar, Fort Collins, CO 80526

©2025 Tolmar. All rights reserved. Tolmar, FENSOLVI, and associated logos, are trademarks of the Tolmar group.

04006226 Rev. 3 09/2025

Medication Guide

FENSOLVI® (fen-SOL-vee)
(leuprolide acetate)
injectable suspension, for subcutaneous use

What is the most important information I should know about FENSOLVI?

FENSOLVI may cause serious side effects, including:

- In the first few weeks after your child receives their first FENSOLVI injection, FENSOLVI can cause an increase in some hormones. During this time, you may notice more signs of puberty in your child including vaginal bleeding. Call your child’s healthcare provider if signs of puberty continue after 2 months of receiving FENSOLVI.

- Some people taking gonadotropin releasing hormone (GnRH) agonists like FENSOLVI have had new or worsened mental (psychiatric) problems. Mental (psychiatric) problems may include emotional symptoms such as:
  - crying
  - irritability
  - restlessness (impatience)
  - anger
  - acting aggressively

Call your child’s healthcare provider right away if your child has any new or worsening emotional symptoms while taking FENSOLVI.

- Some people taking GnRH agonists like FENSOLVI have had seizures. The risk of seizures may be higher in people who:
  - have a history of seizures
  - have a history of epilepsy
  - have a history of brain tumors or brain vessel (cerebrovascular) problems
  - are taking a medicine that has been associated with seizures such as bupropion or selective serotonin reuptake inhibitors (SSRIs)

Seizures have also happened in people who have not had any of these problems.

Call your child’s healthcare provider right away if your child has a seizure while taking FENSOLVI.

- Severe cutaneous (skin) adverse reactions can happen during treatment with GnRH agonists like FENSOLVI. Stop FENSOLVI and call your child’s healthcare provider right away if your child has any of the following signs or symptoms during treatment with FENSOLVI:
  - skin rash or acne
  - dry skin
  - itching
  - blisters on your skin
  - redness or swelling of your face, hands, or soles of your feet
  - blisters or sores in your mouth
  - peeling of your skin
  - fever
  - muscle or joint aches
  - swollen glands
- Increased pressure in the fluid around the brain can happen in children taking GnRH agonists medicines including FENSOLVI. Call your child’s doctor right away if your child has any of the following symptoms during treatment with FENSOLVI:
-
  - headache
  - eye problems, including blurred vision, double vision and decreased eyesight
  - eye pain
  - ringing in the ears
  - dizziness
  - nausea

What is FENSOLVI?

- FENSOLVI is a prescription gonadotropin releasing hormone (GnRH) medicine used for the treatment of children with central precocious puberty (CPP).
- It is not known if FENSOLVI is safe and effective in children younger than 2 years of age.

FENSOLVI should not be received if your child is:

- allergic to GnRH, GnRH agonist medicines, or any ingredients in FENSOLVI. See the end of this Medication Guide for a complete list of ingredients in FENSOLVI.
  Call your child’s healthcare provider or get emergency medical help right away if your child gets any of the following symptoms of a serious allergic reaction:

• skin rashes, redness, or swelling

• swelling of face, mouth, and tongue

• trouble breathing or swallowing

• hives

• throat tightness, hoarseness

• sweating

• severe itching

• dizziness or fainting

• fast heartbeat

- pregnant or becomes pregnant. FENSOLVI can cause birth defects or loss of the baby. If your child becomes pregnant, call your healthcare provider.

Before your child receives FENSOLVI, tell your child’s healthcare provider about all of your child’s medical conditions, including if they:

- have a history of mental (psychiatric) problems.
- have a history of seizures.
- have a history of epilepsy.
- have a history of brain vessel (cerebrovascular) problems.
- have a history of brain or spinal cord (central nervous system) problems or tumors.
- are breastfeeding or plan to breastfeed. It is not known if FENSOLVI passes into breastmilk.

Tell your healthcare provider about all the medicines your child takes, including prescription and over-the-counter medicines, vitamins, and herbal supplements.

How will your child receive FENSOLVI?

- FENSOLVI will be given to your child by a healthcare provider.
- FENSOLVI is injected under the skin (subcutaneous) every 6 months.
- Keep all scheduled visits to the healthcare provider. If you miss a scheduled dose, your child may start having signs of puberty again. The healthcare provider will do regular exams and blood tests to check for signs of puberty.

What are the possible side effects of FENSOLVI?
FENSOLVI may cause serious side effects. See “What is the most important information I should know about FENSOLVI?”

The most common side effects of FENSOLVI include:

• injection site pain

• abdominal pain

• sudden shortness of breath
or wheezing (bronchospasm)

• nasal congestion, sore throat,
and runny nose (nasopharyngitis)

• nausea

• productive cough

• fever (pyrexia)

• constipation

• sudden strong feelings of heat and sweating (hot flush)

• headache

• vomiting

• cough

• upper respiratory tract infection

These are not all the possible side effects of FENSOLVI. Call your healthcare provider for medical advice about side effects. You may report side effects to FDA at 1-800-FDA-1088.

General information about the safe and effective use of FENSOLVI.
Medicines are sometimes prescribed for purposes other than those listed in a Medication Guide.
You can ask your pharmacist or healthcare provider for information about FENSOLVI that is written for health professionals.

What are the ingredients in FENSOLVI?
Active ingredient: leuprolide acetate.
Inactive ingredients: poly (DL-lactide-co-glycolide) and N-methyl-2-pyrrolidone.

Manufactured by:
Tolmar, Fort Collins, CO 80526

©2025 Tolmar
For more information, go to www.fensolvi.com or call 1-888-FENSOLVI (1-888-336-7658).

04006226 Rev. 3 09/2025

This Medication Guide has been approved by the U.S. Food and Drug Administration Revised: 09/2025

INSTRUCTIONS FOR USE

Follow the detailed instructions below to ensure correct preparation of Fensolvi prior to administration:

Step 1

Use aseptic technique including gloves for reconstitution and administration. Allow the product to reach room temperature before reconstitution to allow for easier administration. Administer the product within 30 minutes or discard.
On a clean field open the tray by tearing off the foil from the corner and remove the contents. Discard the desiccant pack. Remove the pre-connected syringe system
from the tray. Open the sterile safety needle package by peeling back the paper tab. Note: Syringe A and Syringe B should not be lined-up yet. The product should only be
administered with the co-packaged, sterile safety needle.

Step 2

Grasp the latching button on the coupling device with your finger and thumb and press until you hear a snapping sound. The two syringes will be aligned.

Do not bend the pre-connected syringe system.

Step 3

Holding the syringes in a horizontal position, transfer the liquid contents of Syringe A into the leuprolide acetate powder contained in Syringe B. Thoroughly mix the product for 60 cycles by pushing the contents back and forth between both syringes to obtain a uniform suspension.

- A cycle is one push of the Syringe A plunger and one push of the Syringe B plunger.
- When thoroughly mixed, the suspension will appear colorless to pale yellow.

Note: Product must be mixed as described; shaking will NOT provide adequate mixing. Do not bend.

Step 4

After mixing, hold the syringes vertically (upright) with Syringe B (wide syringe) on the bottom. The syringes should remain securely coupled. Transfer all of the mixed product into Syringe B by depressing the Syringe A plunger and slightly withdrawing the Syringe B plunger.

Step 5

While ensuring the Syringe A plunger is fully pushed down, hold the coupling device and unscrew Syringe B. This will disconnect Syringe B from the coupling device. Syringe A will remain attached to the coupling device.

Note: Small air bubbles will remain in the formulation – this is acceptable.

Do not purge the air bubbles from Syringe B as product may be lost!

Step 6

Continue to hold Syringe B upright with the open end at the top. Hold back the white plunger on Syringe B to prevent loss of the product, and attach the safety needle and cap (the safety needle is located under the tray). Gently screw clockwise with approximately a three-quarter turn until the safety needle and cap are secure.

Do not overtighten, as the needle hub may become damaged which could result in leakage of the product during injection. The safety shield may also be damaged if the safety needle and cap are screwed with too much force.

Step 7

Move the safety shield away from the needle and towards the syringe.

Pull off the cap immediately prior to administration.

Note: Should the needle hub appear to be damaged, or leak, do not use the product. If the needle hub is damaged or leakage is observed, use a new FENSOLVI carton.

Follow the detailed instructions below to ensure correct administration of FENSOLVI:

1. Select an injection site on the abdomen, upper buttocks, or another location with adequate amounts of subcutaneous tissue that does not have excessive pigment, nodules, lesions, or hair and hasn’t recently been used.

2. Cleanse the injection-site area with an alcohol swab (not enclosed).

3. Using the thumb and forefinger, grab and bunch the area of skin around the injection site.

4. Using your dominant hand, insert the needle quickly at a 90° angle to the skin surface. The depth of penetration will depend on the amount and fullness of the subcutaneous tissue and the length of the needle. After the needle is inserted, release the skin.

5. Inject the drug using a slow, steady push and press down on the plunger until the syringe is empty.

Make sure all the drug has been injected before removing the needle.

6. Withdraw the needle quickly at the same 90° angle used for insertion.

7. Immediately following the withdrawal of the needle, activate the safety shield using a finger/thumb or flat surface and push until it completely covers the needle tip and locks into place.

8. An audible and tactile “click” verifies a locked position.

9. Check to confirm the safety shield is fully engaged. Discard all components safely in an appropriate biohazard container.

©2025 Tolmar

Manufactured by: Tolmar, Fort Collins, CO 80526 04006226 Rev. 3 09/2025